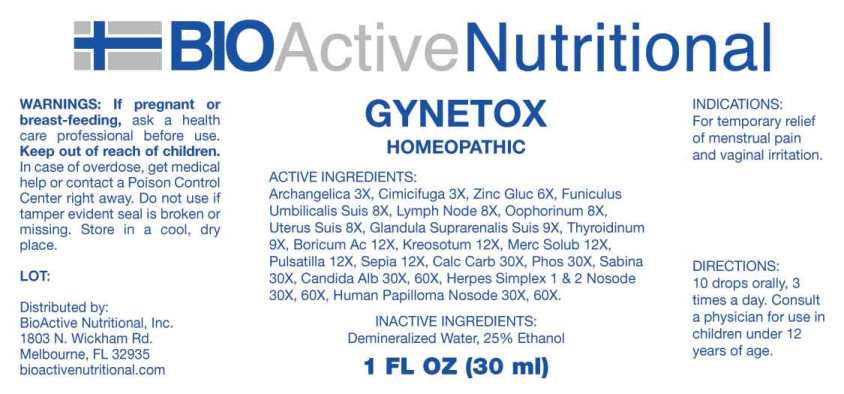 DRUG LABEL: Gynetox
NDC: 43857-0565 | Form: LIQUID
Manufacturer: BioActive Nutritional, Inc.
Category: homeopathic | Type: HUMAN OTC DRUG LABEL
Date: 20241017

ACTIVE INGREDIENTS: ANGELICA ARCHANGELICA ROOT 3 [hp_X]/1 mL; BLACK COHOSH 3 [hp_X]/1 mL; ZINC GLUCONATE 6 [hp_X]/1 mL; SUS SCROFA UMBILICAL CORD 8 [hp_X]/1 mL; SUS SCROFA LYMPH 8 [hp_X]/1 mL; SUS SCROFA OVARY 8 [hp_X]/1 mL; SUS SCROFA UTERUS 8 [hp_X]/1 mL; SUS SCROFA ADRENAL GLAND 9 [hp_X]/1 mL; THYROID 9 [hp_X]/1 mL; BORIC ACID 12 [hp_X]/1 mL; WOOD CREOSOTE 12 [hp_X]/1 mL; MERCURIUS SOLUBILIS 12 [hp_X]/1 mL; PULSATILLA VULGARIS WHOLE 12 [hp_X]/1 mL; SEPIA OFFICINALIS JUICE 12 [hp_X]/1 mL; OYSTER SHELL CALCIUM CARBONATE, CRUDE 30 [hp_X]/1 mL; PHOSPHORUS 30 [hp_X]/1 mL; JUNIPERUS SABINA LEAFY TWIG 30 [hp_X]/1 mL; CANDIDA ALBICANS 30 [hp_X]/1 mL; HUMAN HERPESVIRUS 1 30 [hp_X]/1 mL; HUMAN HERPESVIRUS 2 30 [hp_X]/1 mL; HUMAN PAPILLOMAVIRUS 30 [hp_X]/1 mL
INACTIVE INGREDIENTS: WATER; ALCOHOL

DRUG FACTS:

ACTIVE INGREDIENTS:

Angelica Archangelica, Cimicifuga Racemosa, Zincum Gluconicum, Funiculus Umbilicalis Suis, Lymph Node (Suis), Oophorinum (Suis), Uterus (Suis), Glandula Suprarenalis Suis, Thyroidinum Suis, Boricum Acidum, Kreosotum, Mercurius Solubilis, Pulsatilla (Pratensis), Sepia, Calcarea Carbonica, Phosphorus, Sabina, Candida Albicans, Herpes Simplex 1 And 2 Nosode, Human Papilloma Nosode

INDICATIONS:

For temporary relief of menstrual pain and vaginal irritation.

WARNINGS:

If pregnant or breast-feeding, ask a health care professional before use.

Keep out of reach of children. In case of overdose, get medical help or contact a Poison Control Center right away.

Do not use if tamper evident seal is broken or missing.

Store in cool, dry place.

Keep out of reach of children. In case of overdose, get medical help or contact a Poison Control Center right away.

DIRECTIONS:

10 drops orally, 3 times a day. Consult a physician for use in children under 12 years of age.

INDICATIONS:

For temporary relief of menstrual pain and vaginal irritation.

INACTIVE INGREDIENTS:

Demineralized Water, 25% Ethanol

QUESTIONS:

Distributed by:
BioActive Nutritional, Inc.
1803 N. Wickham Rd.
Melbourne, FL 32935
bioactivenutritional.com

PACKAGE LABEL DISPLAY:

BIOActive Nutritional
GYNETOX
HOMEOPATHIC
1 FL OZ (30 ml)